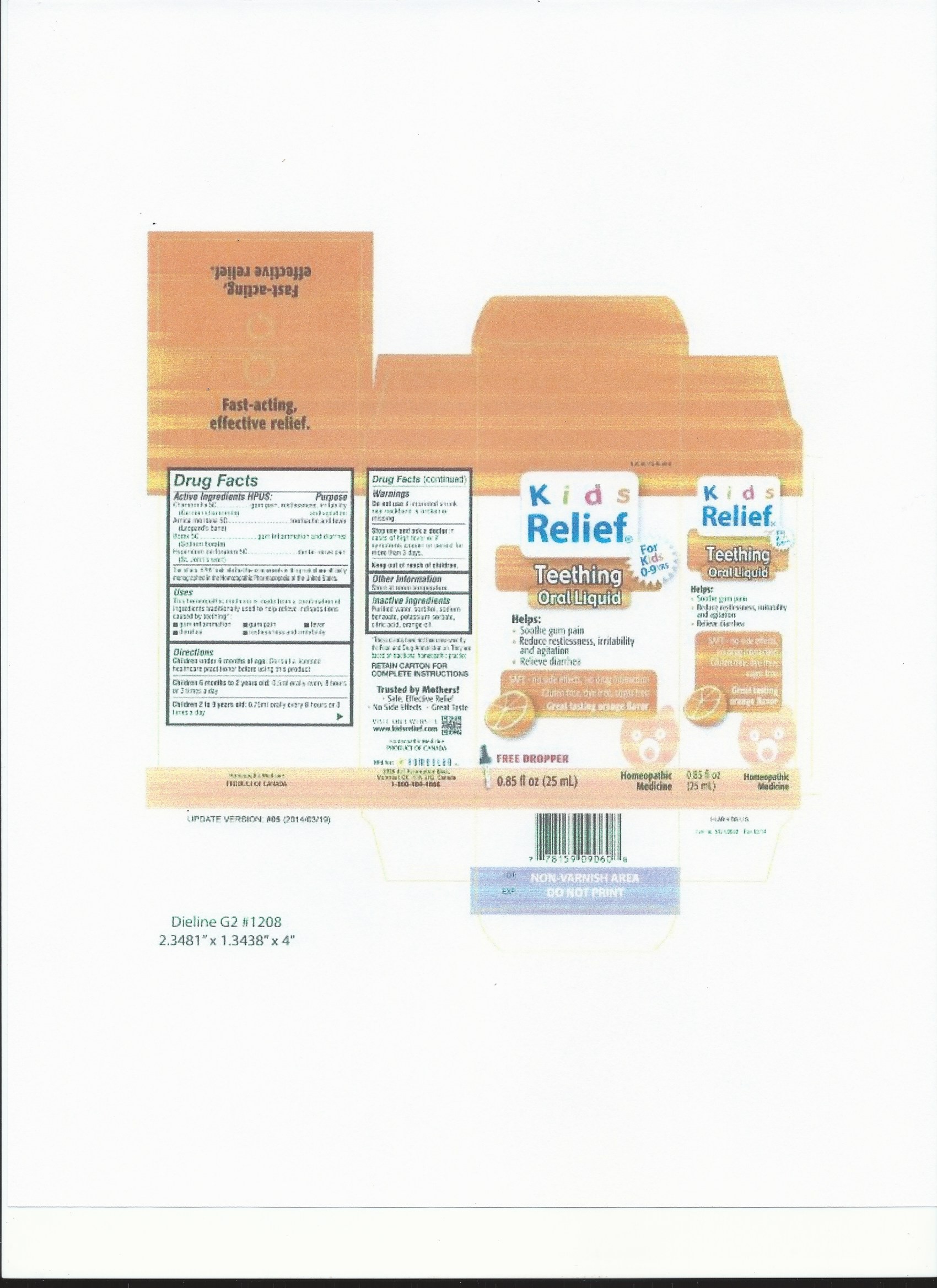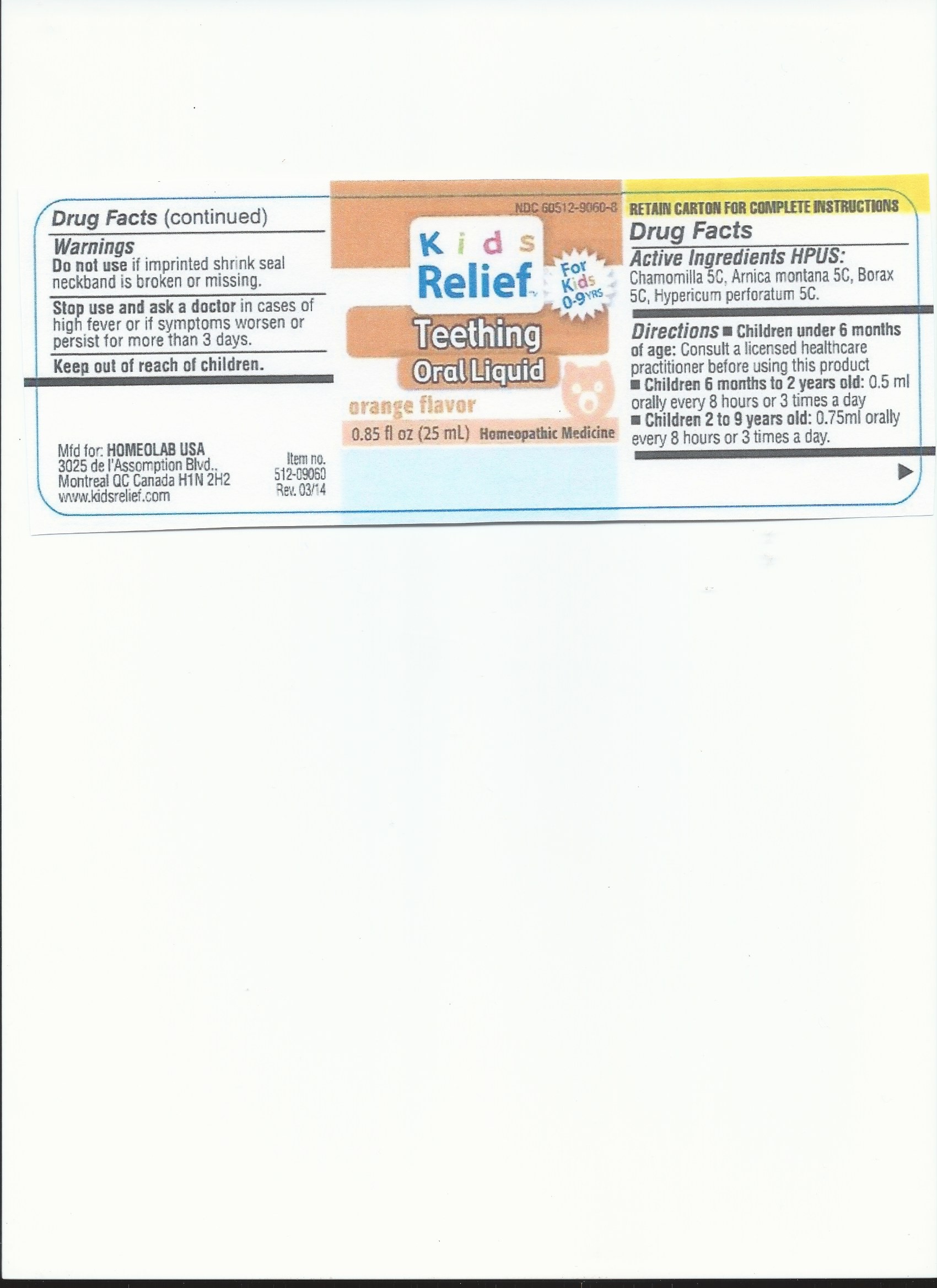 DRUG LABEL: Kids Relief
NDC: 71971-9060 | Form: LIQUID
Manufacturer: Homeolab International (Canada) inc
Category: homeopathic | Type: HUMAN OTC DRUG LABEL
Date: 20190716

ACTIVE INGREDIENTS: MATRICARIA RECUTITA 5 [hp_C]/25 mL; ARNICA MONTANA 5 [hp_C]/25 mL; SODIUM BORATE 5 [hp_C]/25 mL; HYPERICUM PERFORATUM 5 [hp_C]/25 mL
INACTIVE INGREDIENTS: WATER; SORBITOL; SODIUM BENZOATE; POTASSIUM SORBATE; CITRIC ACID MONOHYDRATE

Active Ingredients HPUS:

Chamomilla (German chamomile) 5C

Arnica montana (Leopard's bane) 5C

Borax (Sodium borate) 5C

Hypericum perforatum (St John's wort) 5C

Purpose

Gum pain, restlessness, irritability and agitation

Toothache and fever

Gum inflammation and diarrhea

Dental nerve pain

The letters 'HPUS' indicate that the components in this product are officially monographed in the Homoeopathic Pharmacopoeia of the United States.

Uses

This homeopathic medicine is made from a combination of ingredients traditionally used to help relieve indispositions caused by teething*:

• gum inflammation

• gum pain

• fever

• diarrhea

• restlessness and irritability

Warnings

Do not use if imprinted shrink seal neckband is broken or missing.

Stop use and ask a doctor in cases of high fever or if symptoms worsen or persist for more than 3 days.

Keep out of reach of children.

Directions

Children under 6 months of age: Consult a licensed healthcare practitioner before using this product.

Children 6 months to 2 years old: 0.5 ml orally every 8 hours or 3 times a day.

Children 2 to 9 years old: 0.75 ml orally every 8 hours or 3 times a day.

Other Information

Store at room temperature.

Inactive Ingredients

Purified water, sorbitol, sodium benzoate, potassium sorbate, citric acid, orange oil.

LABEL

PACKAGE LABEL

CARTON